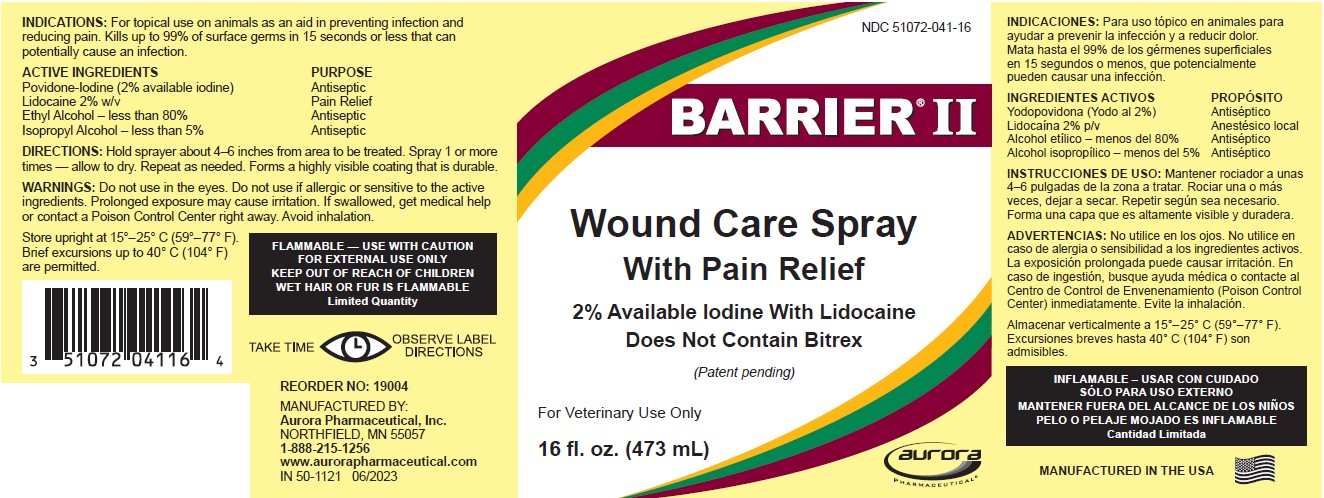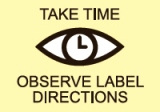 DRUG LABEL: Barrier II Wound Care
NDC: 51072-041 | Form: SOLUTION
Manufacturer: Aurora Pharmaceutical, Inc.
Category: animal | Type: OTC ANIMAL DRUG LABEL
Date: 20251222

ACTIVE INGREDIENTS: Povidone-Iodine 2 g/100 mL; Lidocaine 2 g/100 mL; ALCOHOL 80 mL/100 mL; ISOPROPYL ALCOHOL 5 mL/100 mL

BARRIER II®
Wound Care Spray With Pain Relief

INDICATIONS

For topical use on animals as an aid in preventing infection and reducing pain. Kills up to 99% of surface germs in 15 seconds or less that can potentially cause an infection.

DESCRIPTION

ACTIVE INGREDIENTS | PURPOSE
Povidone-Iodine (2% available iodine) | Antiseptic
Lidocaine 2% w/v | Pain Relief
Ethyl Alcohol – less than 80% | Antiseptic
Isopropyl Alcohol – less than 5% | Antiseptic

DIRECTIONS

Hold sprayer about 4-6 inches from area to be treated. Spray 1 or more times - allow to dry. Repeat as needed. Forms a highly visible coating that is durable.

WARNINGS

Do not use in the eyes. Do not use if allergic or sensitive to the active ingredients. Prolonged exposure may cause irritation. If swallowed, get medical help or contact a Poison Control Center right away. Avoid inhalation.

STORAGE AND HANDLING

Store upright at 15°–25° C (59°–77° F). Brief excursions up to 40° C (104° F) are permitted.

BOXED WARNING

FLAMMABLE — USE WITH CAUTION
FOR EXTERNAL USE ONLY
KEEP OUT OF REACH OF CHILDREN
WET HAIR OR FUR IS FLAMMABLE

Limited Quantity

REORDER

NO: 19004

MANUFACTURED BY:
Aurora Pharmaceutical, Inc.
NORTHFIELD, MN 55057
1-888-215-1256
www.aurorapharmaceutical.com

IN 50-1121 06/2023

MANUFACTURED IN THE USA

PRINCIPAL DISPLAY PANEL - 473 ml Bottle Label

NDC 51072-041-16

BARRIER II®

Wound Care Spray

With Pain Relief

2% Available Iodine with Lidocaine

Does Not Contain Bitrex

(Patent pending)

For Veterinary Use Only

16 fl. oz. (473 ml)

AURORA PHARMACEUTICAL ®